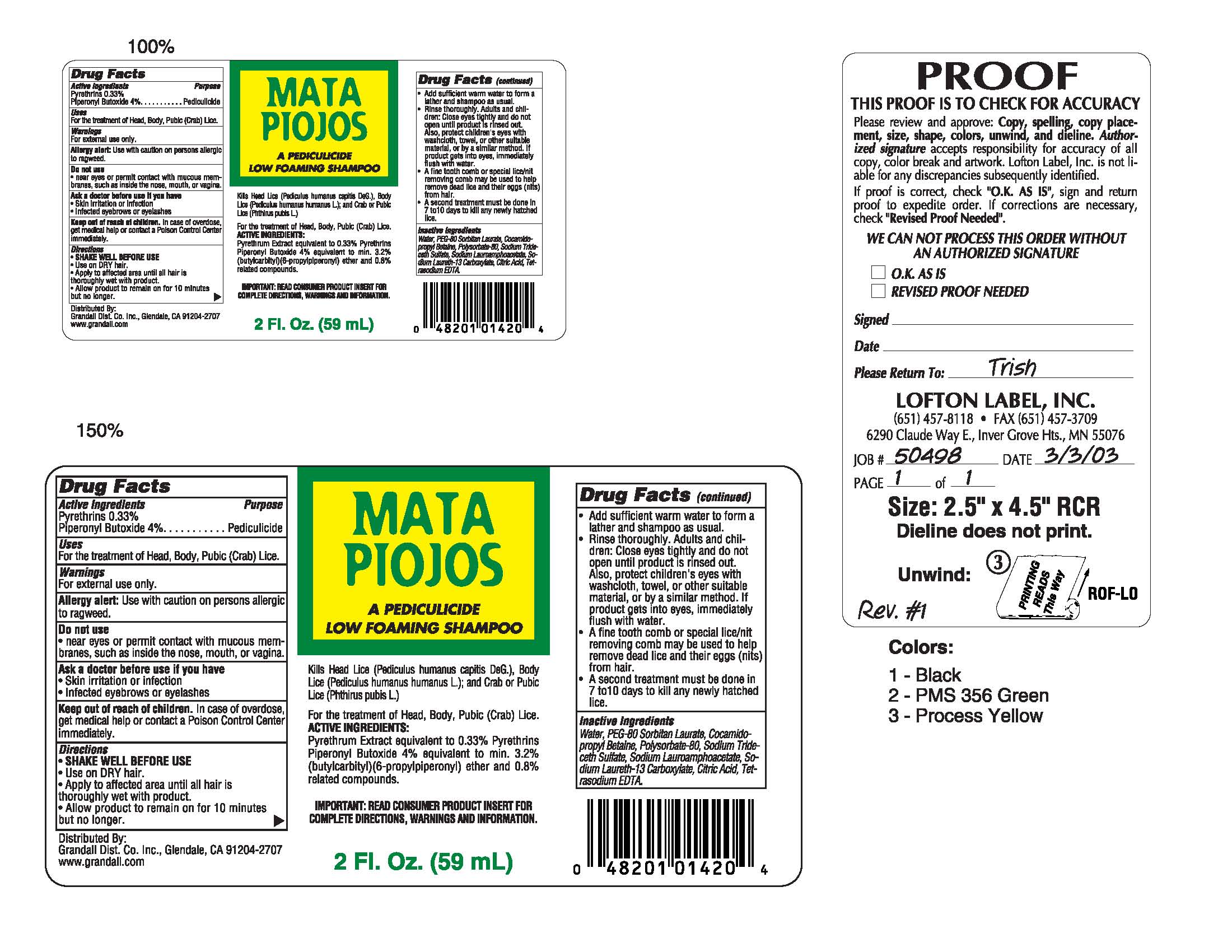 DRUG LABEL: Mata Piojos
NDC: 57501-865 | Form: SHAMPOO
Manufacturer: Apex International Mfg
Category: otc | Type: HUMAN OTC DRUG LABEL
Date: 20100423

ACTIVE INGREDIENTS: Pyrethrum Extract .12 g/60 g; Piperonyl Butoxide 2.4 g/60 g
INACTIVE INGREDIENTS: Water 39.78 g/60 g; COCAMIDOPROPYL BETAINE 14.2 g/60 g; POLYSORBATE 80 3.5 g/60 g

Drug Facts

Drug Facts

Active Ingredients Purpose
Pyrethrins 0.33%
Piperonyl Butoxide 4%........Pedicullicide
Uses
For the treatment of Head, Body, Pubic (Crab) Lice.
Warnings
For external use only.
Allergy alert:
Use with caution on persons allergic to ragweed.
Do not use

- near eyes or permit contact with mucous membranes, such as inside the nose, mouth, or vagina.

Ask a doctor before use if you have

- Skin irritation or infection
- Infected eyebrows or eyelashes

Keep out of reach of children.
In case of overdose, get medical help or contact a Poison Control Center immediately.
Directions

- SHAKE WELL BEFORE USE
- Use on DRY hair.
- Apply to affected area until all hair is thoroughly wet with product
- Allow product to remain on for 10 minutes but no longer.

ACTIVE INGREDIENTS:

Pyrethrum Extract equivalent to 0.33% Pyrethrins

Piperonyl Butoxide 4% equivalent to min. 3.2%

(butylcarbityl)(6-propylpiperonyl) ether and 0.8% related compounds.